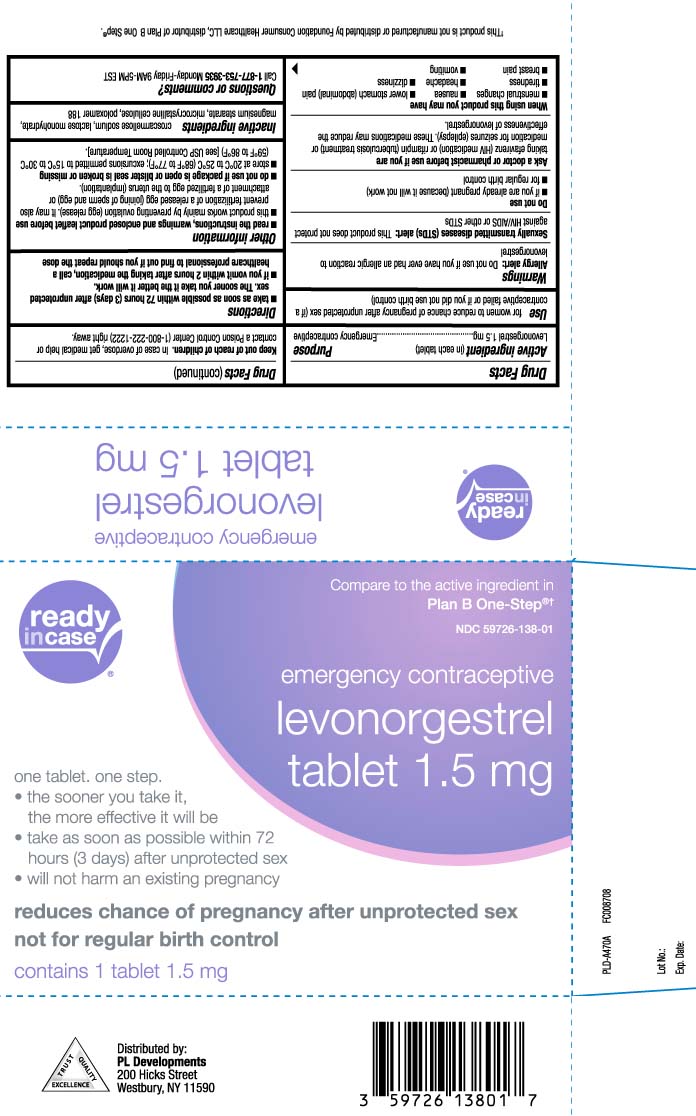 DRUG LABEL: Emergency Contraceptive
NDC: 59726-138 | Form: TABLET
Manufacturer: P & L Development, LLC
Category: otc | Type: HUMAN OTC DRUG LABEL
Date: 20230627

ACTIVE INGREDIENTS: LEVONORGESTREL 1.5 mg/1 1
INACTIVE INGREDIENTS: CROSCARMELLOSE SODIUM; LACTOSE MONOHYDRATE; MAGNESIUM STEARATE; MICROCRYSTALLINE CELLULOSE; POLOXAMER 188

EContra One-Step®
(Levonorgestrel) Tablet 1.5 mg

Active ingredient (in each tablet)

Levonorgestrel 1.5 mg

Purpose

Emergency contraceptive

Use

for women to reduce chance of pregnancy after unprotected sex (if a contraceptive failed or if you did not use birth control)

Warnings

Allergy alert: Do not use if you have ever had an allergic reaction to levonorgestrel
Sexually transmitted diseases (STDs) alert: This product does not protect against HIV/AIDS or other STDs

Do not use

- if you are already pregnant (because it will not work)
- for regular birth control

Ask a doctor or pharmacist before use if you are

taking efavirenz (HIV medication) or rifampin (tuberculosis treatment) or medication for seizures (epilepsy). These medications may reduce the effectiveness of levonorgestrel.

When using this product you may have

- menstrual changes
- tiredness
- breast pain
- nausea
- headache
- vomiting
- lower stomach (abdominal) pain
- dizziness

Keep out of reach of children

In case of overdose, get medical help or contact a Poison Control Center (1-800-222-1222) right away.

Directions

- take as soon as possible within 72 hours (3 days) after unprotected sex. The sooner you take it the better it will work.
- if you vomit within 2 hours after taking the medication, call a healthcare professional to find out if you should repeat the dose.

Other information

- read the instructions, warnings and enclosed product leaflet before use
  - this product works mainly by preventing ovulation (egg release). It may also prevent fertilization of a release egg (joining of sperm and egg) or attachment of a fertilized egg to the uterus (implantation)
- do not use if package is open or blister seal is broken or missing
- store at 20ºC to 25ºC (68ºF to 77ºF); excursions permitted to 15ºC to 30ºC (59ºF to 86ºF) [see USP Controlled Room Temperature].

Inactive ingredients

croscarmellose sodium, lactrose monohydrate, magnesium stearate, microcrystalline cellulose, poloxamer 188

Questions or comments?

Call 1-877-753-3935 Monday-Friday 9AM-5PM EST

Principal display panel

Compare to the active ingredient in Plan B One-Step®†

emergency contraceptive

levonorgestrel

Tablet 1.5 mg

one tablet. one step.

- the sooner you take it, the more effective it will be
- take as soon as possible within 72 hours (3 days) after unprotected sex
- will not harm an existing pregnancy

reduces chance of pregnancy after unprotected sex not for regular birth control

tablet 1.5 mg

†This product is not manufactured or distributed by Foundation Consumer Healthcare LLC, distributor of Plan B One Step®.

Distributed by:

PL Developments

200 Hicks Street

Westbury, NY 11590

Package Label

READYinCASE Emergency Contraceptive